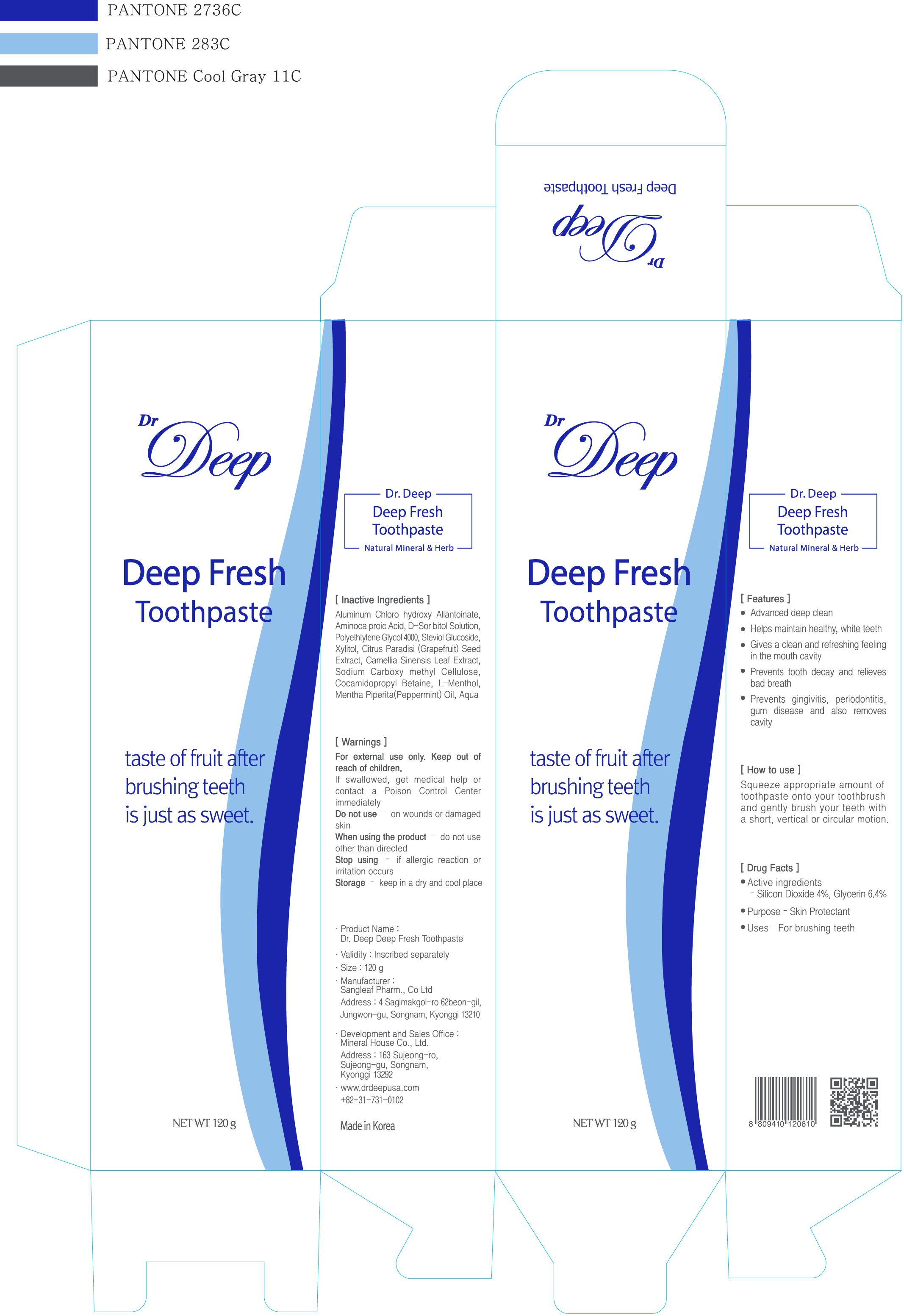 DRUG LABEL: Dr Deep Deep Fresh
NDC: 76015-110 | Form: PASTE, DENTIFRICE
Manufacturer: MineralHouse Corporation
Category: otc | Type: HUMAN OTC DRUG LABEL
Date: 20160812

ACTIVE INGREDIENTS: GLYCERIN 7.68 g/120 g
INACTIVE INGREDIENTS: SILICON DIOXIDE 4.8 g/120 g; ALCLOXA; AMINOCAPROIC ACID; SORBITOL; POLYETHYLENE GLYCOL 4000; XYLITOL; CITRUS PARADISI SEED; GREEN TEA LEAF; CARBOXYMETHYLCELLULOSE; COCAMIDOPROPYL BETAINE; LEVOMENTHOL; MENTHA PIPERITA; WATER

Active Ingredient: Silicon Dioxide 4%, Glycerin 6.4%

INDICATIONS AND USAGE

Squeeze appropriate amount of toothpaste onto your toothbrush and gently brush your teeth with a short, vertical or circular motion

DOSAGE AND ADMINISTRATION

For brushing teeth

Purpose: Skin Protectant

Warnings:

- For external use only

- Do not use on wounds or damaged skin

When using this product, do not use other than directed

Stop use if allergic reaction or irritation occurs

Keep out of reach of children

- If swallowed, get medical help or contact a Poison Control Center immediately

Storage: Keep in a dry and cool place

INACTIVE INGREDIENT

Inactive Ingredients: Aluminum Chlorohydroxy Allantoinate, Aminocaproic Acid, D-Sorbitol Solution, Polyethylene Glycol 4000, stevgiol Glycoside, Xylitol, Citrus Paradisi (Grapefruit) Seed Extract, Camellia Sinensis Leaf Extract, Sodium Carboxymethyl Cellulose, Cacamidopropyl Betaine, L-Menthol, Mentha Piperita (Peppermint) Oil, Aqua